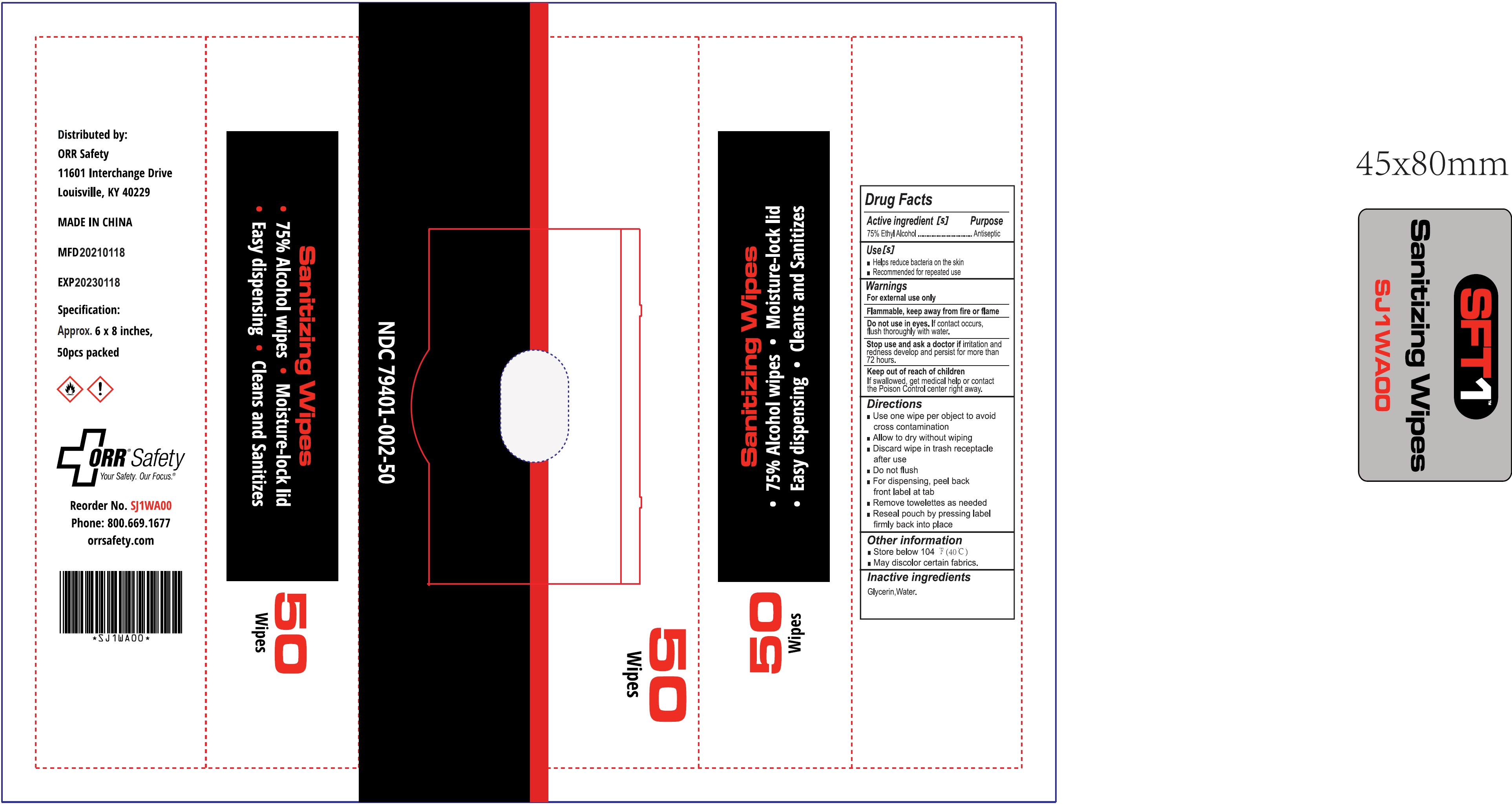 DRUG LABEL: SFT1 Sanitizing Wipes
NDC: 79401-002 | Form: CLOTH
Manufacturer: ORR Safety
Category: otc | Type: HUMAN OTC DRUG LABEL
Date: 20231026

ACTIVE INGREDIENTS: ALCOHOL 0.75 mL/1 mL
INACTIVE INGREDIENTS: GLYCERIN; WATER

SFT1 Sanitizing Wipes

Active ingredient [s]

75% Ethyl Alcohol

Purpose

Antiseptic

Use[s]

- Helps reduce bacteria on the kin
- Recommended for repeated use

Warnings

For external use only. Flammable. keep away from fire or flame

Do not use in eyes.

If contact occurs, flush thoroughly with water.

Stop use and ask a doctor if

irritation and redness develop and persist for more than 72 hours.

Keep out of reach of children.

If swallowed, get medical help or contact a Poison Control Center right away.

Direction

- Use one wipe per object to avoid cross contamination
- Allow to dry without wiping
- Discard wipe in trash receptacle after use
- Do not flush
- For dispending, peel back front label at tab
- Remove pouch by pressing label firmly back into place

Other information

- Store below 104 °F (40 °C)
- May discolor certain fabrics.

Inactive ingredients

Water